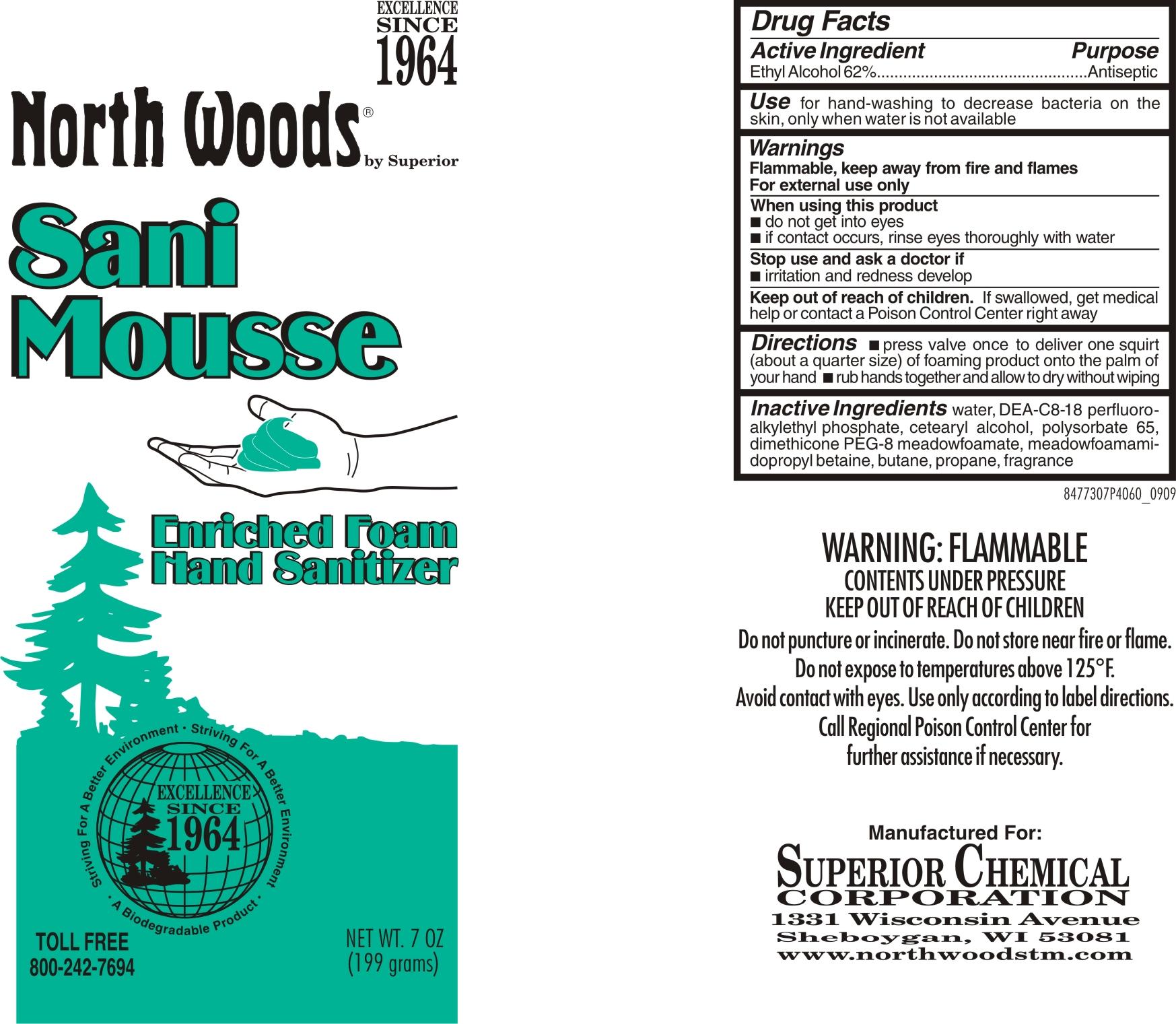 DRUG LABEL: Sani Mousse
                
                
NDC: 53125-773 | Form: AEROSOL, FOAM
Manufacturer: Superior Chemical Corporation
Category: otc | Type: HUMAN OTC DRUG LABEL
Date: 20120904

ACTIVE INGREDIENTS: ALCOHOL 620 mg/1 g
INACTIVE INGREDIENTS: PROPANE; BUTANE; WATER

Sani Mousse 4773 Drug Facts and Label

Drug Facts Box OTC-Active Ingredients Section

Ethyl Alcohol 62%

Drug Facts Box OTC-Purpose Section

Antiseptic

INDICATIONS AND USAGE

for hand-washing to decrease bacteria on the skin, only when water is not available

Drug Facts Box OTC-Warnings Section

Flammable, keep away from fire and flames

For external use only

Drug Facts Box OTC-When Using Section

do not get into eyes

if contact occurs, rinse eyes thoroughly with water

Drug Facts Box OTC-Stop Use Section

irritation and redness develop

Drug Facts Box OTC-Keep Out of Reach of Children Section

If swallowed, get medical help or contact a Poison Control Center right away

Drug Facts Box OTC-Dosage & Administration Section

Press valve once to deliver one squirt (about a quarter size) of foaming product into the palm of your hand

rub hands together and allow to dry without wiping

Drug Facts Box OTC-Inactive Ingredients Section

water, DEA-C8-18 perfluoroalkylethyl phosphate, cetearyl alcohol, polysorbate 65, dimethicone PEG-8 meadowfoamate, meadowfoamamidopropyl betaine, butane, propane, fragrance

Sani Mousse 4773 199g

477307P4060.jpg